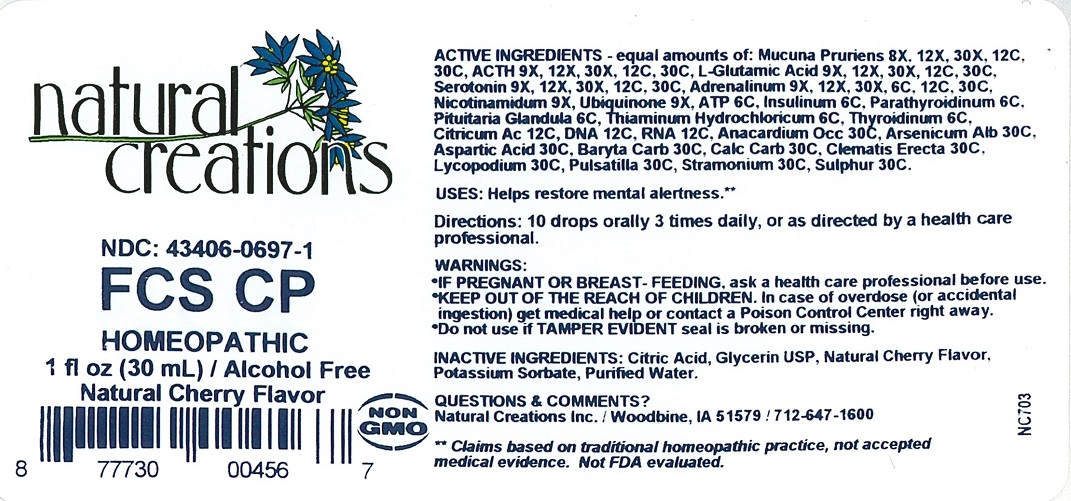 DRUG LABEL: FCS CP
NDC: 43406-0697 | Form: LIQUID
Manufacturer: Natural Creations, Inc
Category: homeopathic | Type: HUMAN OTC DRUG LABEL
Date: 20251210

ACTIVE INGREDIENTS: CORTICOTROPIN 30 [hp_C]/1 mL; GLUTAMIC ACID 30 [hp_C]/1 mL; MUCUNA PRURIENS SEED 30 [hp_C]/1 mL; SEROTONIN 30 [hp_C]/1 mL; EPINEPHRINE 30 [hp_C]/1 mL; NIACINAMIDE 8 [hp_X]/1 mL; UBIDECARENONE 8 [hp_X]/1 mL; ADENOSINE TRIPHOSPHATE 6 [hp_C]/1 mL; INSULIN PORK 6 [hp_C]/1 mL; SUS SCROFA PARATHYROID GLAND 6 [hp_C]/1 mL; SUS SCROFA PITUITARY GLAND 6 [hp_C]/1 mL; THIAMINE HYDROCHLORIDE 6 [hp_C]/1 mL; THYROID, UNSPECIFIED 6 [hp_C]/1 mL; ANHYDROUS CITRIC ACID 12 [hp_C]/1 mL; HERRING SPERM DNA 12 [hp_C]/1 mL; SACCHAROMYCES CEREVISIAE RNA 12 [hp_C]/1 mL; ANACARDIUM OCCIDENTALE FRUIT 30 [hp_C]/1 mL; ARSENIC TRIOXIDE 30 [hp_C]/1 mL; ASPARTIC ACID 30 [hp_C]/1 mL; BARIUM CARBONATE 30 [hp_C]/1 mL; OYSTER SHELL CALCIUM CARBONATE, CRUDE 30 [hp_C]/1 mL; CLEMATIS RECTA FLOWERING TOP 30 [hp_C]/1 mL; LYCOPODIUM CLAVATUM SPORE 30 [hp_C]/1 mL; ANEMONE PULSATILLA 30 [hp_C]/1 mL; DATURA STRAMONIUM 30 [hp_C]/1 mL; SULFUR 30 [hp_C]/1 mL
INACTIVE INGREDIENTS: CITRIC ACID MONOHYDRATE; GLYCERIN; POTASSIUM SORBATE; WATER

FCS CP

ACTIVE INGREDIENT

ACTIVE INGREDIENTS - equal amounts of: Mucuna Pruriens 8X, 12X, 30X, 12C, 30C, ACTH 9X, 12X, 30X, 12C, 30C, L-Glutamic Acid 9X, 12X, 30X, 12C, 30C, Serotonin 9X, 12X, 30X, 12C, 30C, Adrenalinum 9X, 12X, 30X, 6C, 12C, 30C, Nicotinamidum 9X, Ubiquinone 9X, ATP 6C, Insulinum 6C, Parathyroidinum 6C, Pituitaria Glandula 6C, Thiaminum Hydrochloricum 6C, Thyroidinum 6C, Citricum Acidum 12C, DNA 12C, RNA 12C, Anacardium Occ 30C, Arsenicum Alb 30C, Aspartic Acid 30C, Baryta Carb 30C, Calc Carb 30C, Clematis Erecta 30C, Lycopodium 30C, Pulsatilla 30C, Stramonium 30C, Sulphur 30C.

INDICATIONS AND USAGE

USES: Helps restore mental alertness.**

PURPOSE

USES: Helps restore mental alertness.**

DOSAGE AND ADMINISTRATION

DIRECTIONS: 10 drops orally 3 times daily, or as directed by a health care professional.

KEEP OUT OF REACH OF CHILDREN

KEEP OUT OF THE REACH OF CHILDREN. In case of overdose (or accidental ingestion) get medical help or contact a Poison Control Center right away.

WARNINGS:

- IF PREGNANT OR BREAST-FEEDING, ask a health care professional before use.
- KEEP OUT OF THE REACH OF CHILDREN. In case of overdose (or accidental ingestion) get medical help or contact a Poison Control Center right away.
- Do not use if Tamper Evident seal is broken or missing.

INACTIVE INGREDIENT

INACTIVE INGREDIENTS: Citric Acid, Glycerin USP, Natural Cherry Flavor, Potassium Sorbate, Purified Water.

QUESTIONS & COMMENTS?

Natural Creations, Inc. / Woodbine, IA 51579 / 712-647-1600

REFERENCES

**Claims based on traditional homeopathic practice, not accepted medical evidence. Not FDA evaluated.

PACKAGE LABEL

NDC: 43406-0697-1

FCS CP

HOMEOPATHIC

1 fl oz (30 mL) / Alcohol Free

Natura Cherry Flavor